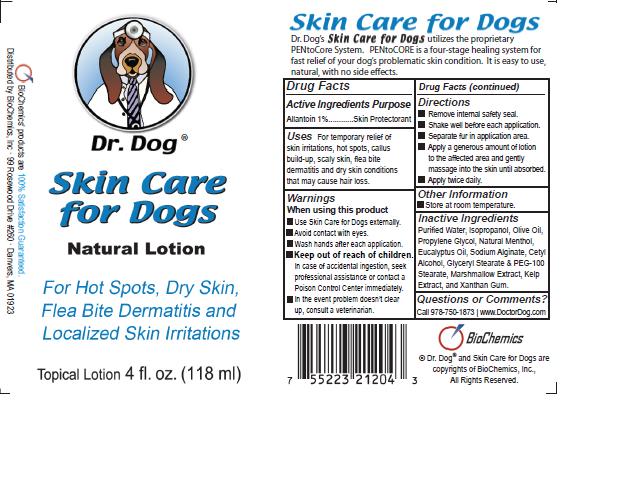 DRUG LABEL: Dr. Dog Skin Care for Dogs
								
NDC: 60608-014 | Form: LOTION
Manufacturer: Bio Chemics
Category: animal | Type: OTC ANIMAL DRUG LABEL
Date: 20110512

ACTIVE INGREDIENTS: ALLANTOIN 5.11 g/118 g
INACTIVE INGREDIENTS: WATER; ISOPROPYL ALCOHOL; OLIVE OIL; PROPYLENE GLYCOL; EUCALYPTUS OIL; SODIUM ALGINATE; CETYL ALCOHOL; GLYCERYL MONOSTEARATE; POLYOXYL 100 STEARATE; SEAWEED; ALTHAEA OFFICINALIS LEAF EXTRACT; MENTHOL; XANTHAN GUM

Drug Facts

Active Ingredient

Allantoin 1%

Purpose

Skin Protectorant

Uses

For temporary relief of skin irritations, hot spots, callus build-up, scaly skin, flea bite dermatitis and dry skin conditions that may cause hair loss.

Warnings

When using this product

■ Use Skin Care for Dogs externally.

■ Avoid contact with eyes.

■ Wash hands after each application.

■ Keep out of reach of children.

In case of accidental ingestion, seek professional assistance or contact a Poison Control Center immediately.

■ In the event problem doesn't clear up, consult a veterinarian.

KEEP OUT OF REACH OF CHILDREN

Enter section text here

DOSAGE AND ADMINISTRATION

■ Remove internal safety seal.

■ Shake well before each application.
■ Separate fur in application area.
■ Apply a generous amount of lotion to the affected area and gently massage into the skin until absorbed.
■ Apply twice daily.
OTHER INFORMATION
■ Store at room temperature.section text here

Inactive Ingredients

Purified Water, Isopropanol, Olive Oil, Propylene Glycol, Natural Menthol, Eucalyptus Oil, Sodium Alginate, Cetyl Alcohol, Glyceryl Stearate and PEG-100 Stearate, Marshmallow Extract, Kelp Extract and Xanthan Gum.

Questions or Comments?

Call 978-750-1873 www.DoctorDog.com

BioChemics

© Dr. Dog and Skin Care for Dogs are copyrights of BioChemics, Inc.

All rights reserved.